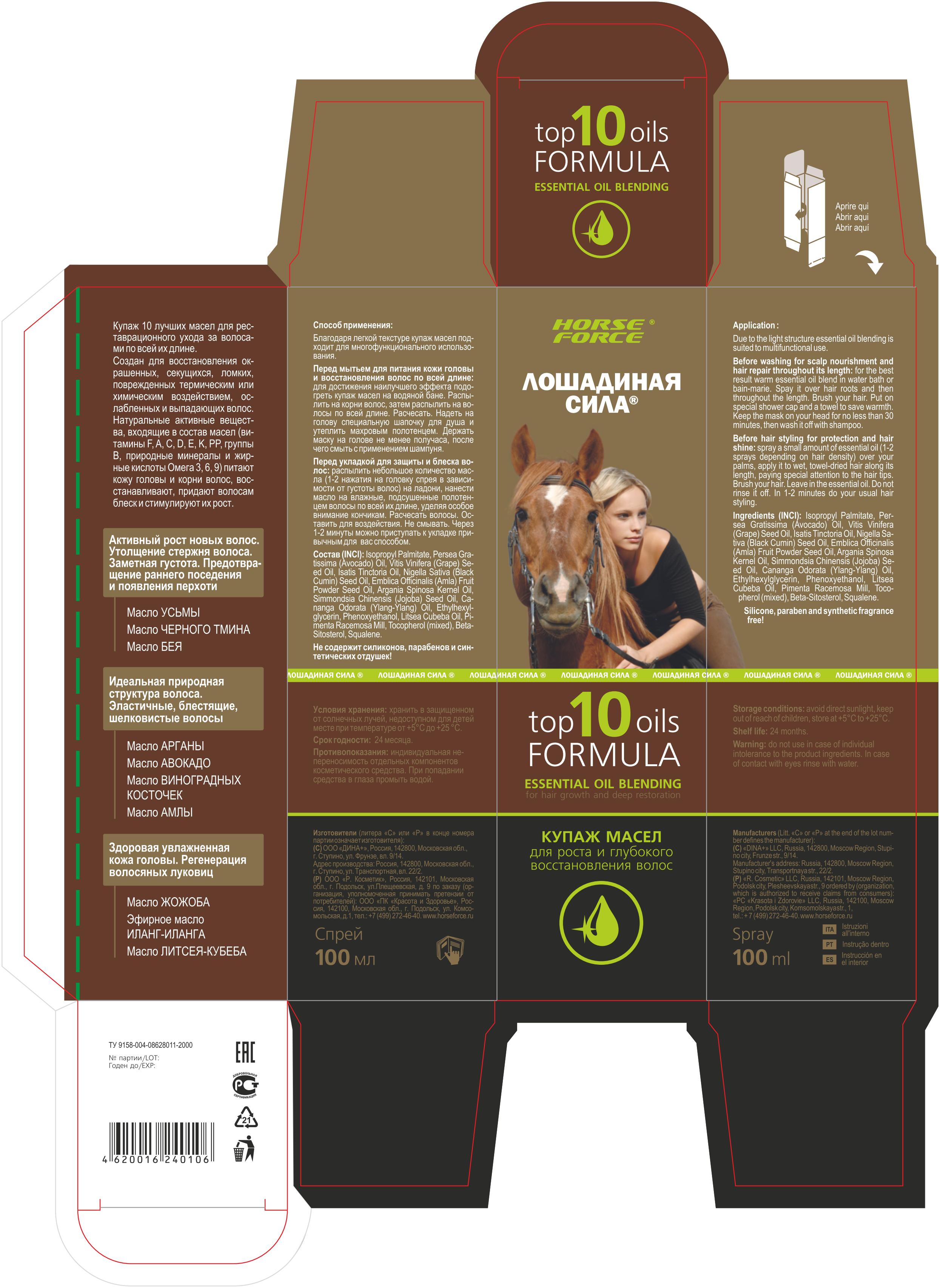 DRUG LABEL: Oil blending for hair growth and deep revitalization TOP 10 OILS FORMULA HORSE FORCE
NDC: 70349-0001 | Form: OIL
Manufacturer: Zeldis-farma, Ooo
Category: otc | Type: HUMAN OTC DRUG LABEL
Date: 20160428

WARNINGS

Storage Condition

Keep Out of reach of children